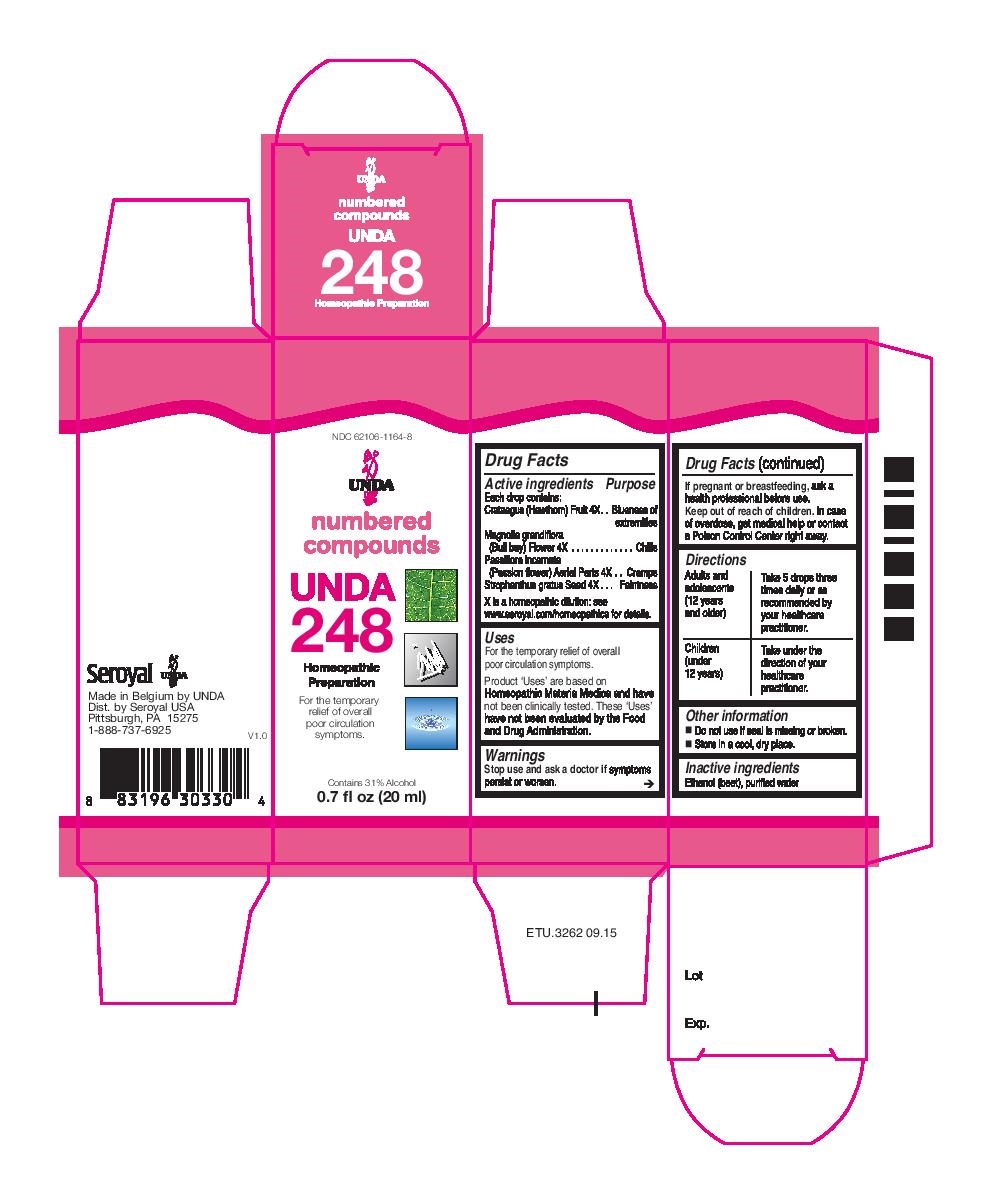 DRUG LABEL: UNDA 248
NDC: 62106-1164 | Form: LIQUID
Manufacturer: Seroyal USA
Category: homeopathic | Type: HUMAN OTC DRUG LABEL
Date: 20221109

ACTIVE INGREDIENTS: STROPHANTHUS GRATUS SEED 4 [hp_X]/20 mL; CRATAEGUS FRUIT 4 [hp_X]/20 mL; MAGNOLIA GRANDIFLORA FLOWER 4 [hp_X]/20 mL; PASSIFLORA INCARNATA FLOWERING TOP 4 [hp_X]/20 mL
INACTIVE INGREDIENTS: ALCOHOL; WATER

UNDA 248

Active ingredients
Each drop contains:
Crataegus (Hawthorn) Fruit 4X
Magnolia grandiflora (Bull bay) Flower 4X
Passiflora incarnata (Passion flower) Aerial Parts 4X
Strophanthus gratus Seed 4X

Uses
For the temporary relief of overall poor circulation symptoms.

Warnings
Stop use and ask a doctor if symptoms persist or worsen.
If pregnant or breastfeeding, ask a health professional before use.
Keep out of reach of children. In case of overdose, get medical help or contact
a Poison Control Center right away.

Keep out of reach of children.

PREGNANCY OR BREAST FEEDING

If pregnant or breastfeeding, ask a health professional before use.

Other information
Do not use if seal is missing or broken.
Store in a cool, dry place.

Inactive ingredients
Ethanol (beet), purified water

Directions
Adults and adolescents (12 years and older)
Take 5 drops three times daily or as
recommended by your healthcare practitioner.

Children (under 12 years)
Take under the direction of your healthcare practitioner.

Uses
For the temporary relief of overall poor circulation symptoms.

Directions
Adults and adolescents (12 years and older)
Take 5 drops three times daily or as recommended by your healthcare practitioner.

Children (under 12 years)
Take under the direction of your healthcare practitioner.

PACKAGE LABEL

NDC 62106-1164-8

UNDA

numbered compounds

UNDA 248

Homeopathic Preparation

For the temporary relief of overall poor circulation symptoms.

Contains 31% Alcohol

0.7 fl oz (20 ml)